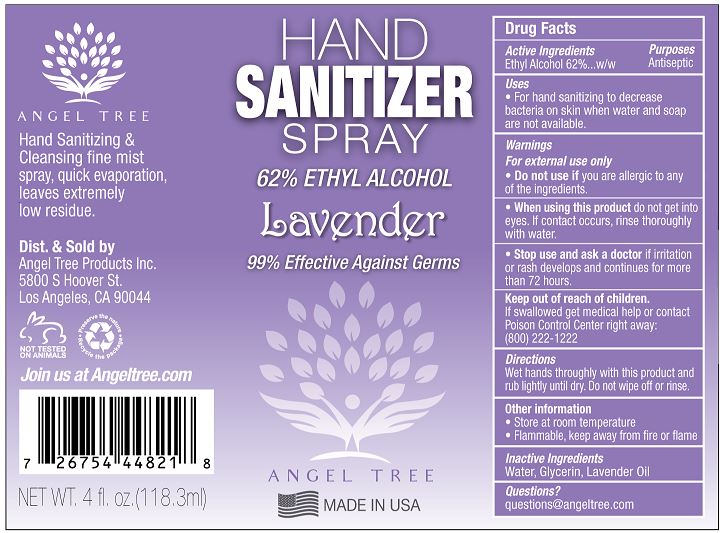 DRUG LABEL: Hand Sanitizer
NDC: 77890-101 | Form: SPRAY
Manufacturer: Angel Tree Products Inc.
Category: otc | Type: HUMAN OTC DRUG LABEL
Date: 20201124

ACTIVE INGREDIENTS: ALCOHOL 62 mL/100 mL
INACTIVE INGREDIENTS: WATER; GLYCERIN; LAVENDER OIL

ANGEL TREE HAND SANITIZER SPRAY, 62% ETHYL ALCOHOL, LAVENDER

Active Ingredient(s)

ETHYL ALCOHOL 62% W/W

Purpose

Antiseptic

Use

- For hand sanitizing to decrease bacteria on skin when water and soap are not available.

Warnings

For external use only.

- Do not use if you are allergic to any of the ingredients.
- When using this product do not get into eyes. If contact occurs, rinse eyes thoroughly with water.
- Stop use and ask a doctor if irritation or rash develops and continues for more than 72 hours.

Keep out of reach of children.

If swallowed, get medical help or contact a Poison Control Center right away: (800) 222-1222

Directions

WET HANDS THOROUGHLY WITH THIS PRODUCT AND RUB LIGHTLY UNTIL DRY. DO NOT WIPE OFF OR RINSE.

Other information

- Store at room temperature
- Flammable, keep away from fire or flame.

Inactive ingredients

WATER, GLYCERIN, LAVENDER OIL

Questions?

questions@angeltree.com